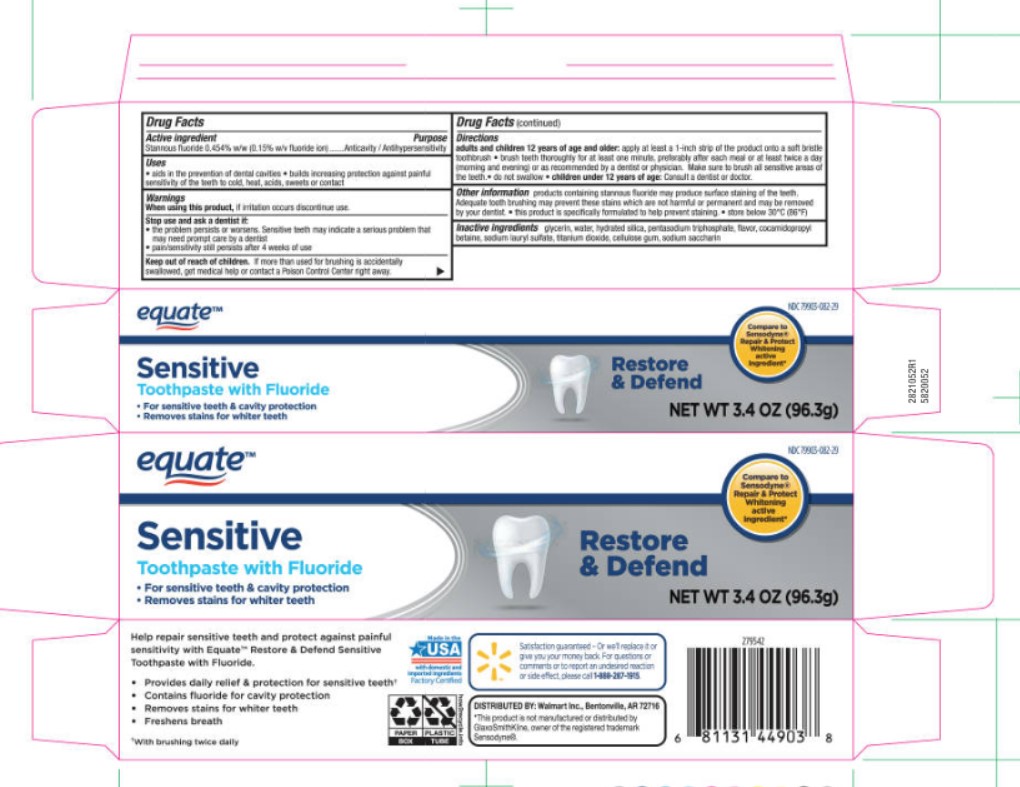 DRUG LABEL: Equate Repair and Protect
NDC: 79903-082 | Form: PASTE, DENTIFRICE
Manufacturer: Walmart
Category: otc | Type: HUMAN OTC DRUG LABEL
Date: 20251113

ACTIVE INGREDIENTS: STANNOUS FLUORIDE 0.15 g/100 g
INACTIVE INGREDIENTS: SODIUM LAURYL SULFATE; WATER; CARBOXYMETHYLCELLULOSE SODIUM; GLYCERIN; SACCHARIN SODIUM; SODIUM TRIPOLYPHOSPHATE ANHYDROUS; TITANIUM DIOXIDE; HYDRATED SILICA; COCAMIDOPROPYL BETAINE

5820052 Sensitive Restore & Defend Whitening (8015274)

ACTIVE INGREDIENT

Stannous fluoride 0.454% w/w (0.15% w/v fluoride ion)

PURPOSE

Anticavity / Antihypersensitivity

INDICATIONS AND USAGE

Aids in the prevention of dental cavities * builds increasing protection against painful sensitivity of the teeth to cold, heat, acids, sweets or contact

When using this product, if irriation occurs discontinue use.

Stop use and ask a dentist if:

- the problem persists or worsens. Sensitive teeth may indicate a serious problem that may need prompt care by a dentist.
- pain/sensitivity still persists after 4 weeks of use.

KEEP OUT OF REACH OF CHILDREN

If more than used for brushing is accidentally swallowed, get medical help or contact a Poison Control Center right away.

DOSAGE AND ADMINISTRATION

adults and children 12 years of age or older: apply at least a 1-inch strip of the product onto a soft bristle toothbrush * brush teeth thoroughly for at least one minute, preferrably after each meal or at least twice a day (morning and evening) or as recommended by a dentist or physician. Make sure to brush all sensitive areas of the teeth. * do not swallow * children under 12 years of age: Consult a dentist or doctor.

OTHER SAFETY INFORMATION

products containing stannous fluoride may produce surface staining of the teeth. Adequade tooth brushing may prevent these stains which are not harmful or permanent and may be removed by your dentist. * this product is specifically formulated to help prevent staining. * store below 30ºC (86ºF)

INACTIVE INGREDIENT

glycerin, water, hydrated silica, pentasodium triphosphate, flavor, cocamidopropyl betaine, sodium lauryl sulfate, titanium dioxide, cellulose gum, sodium saccharin